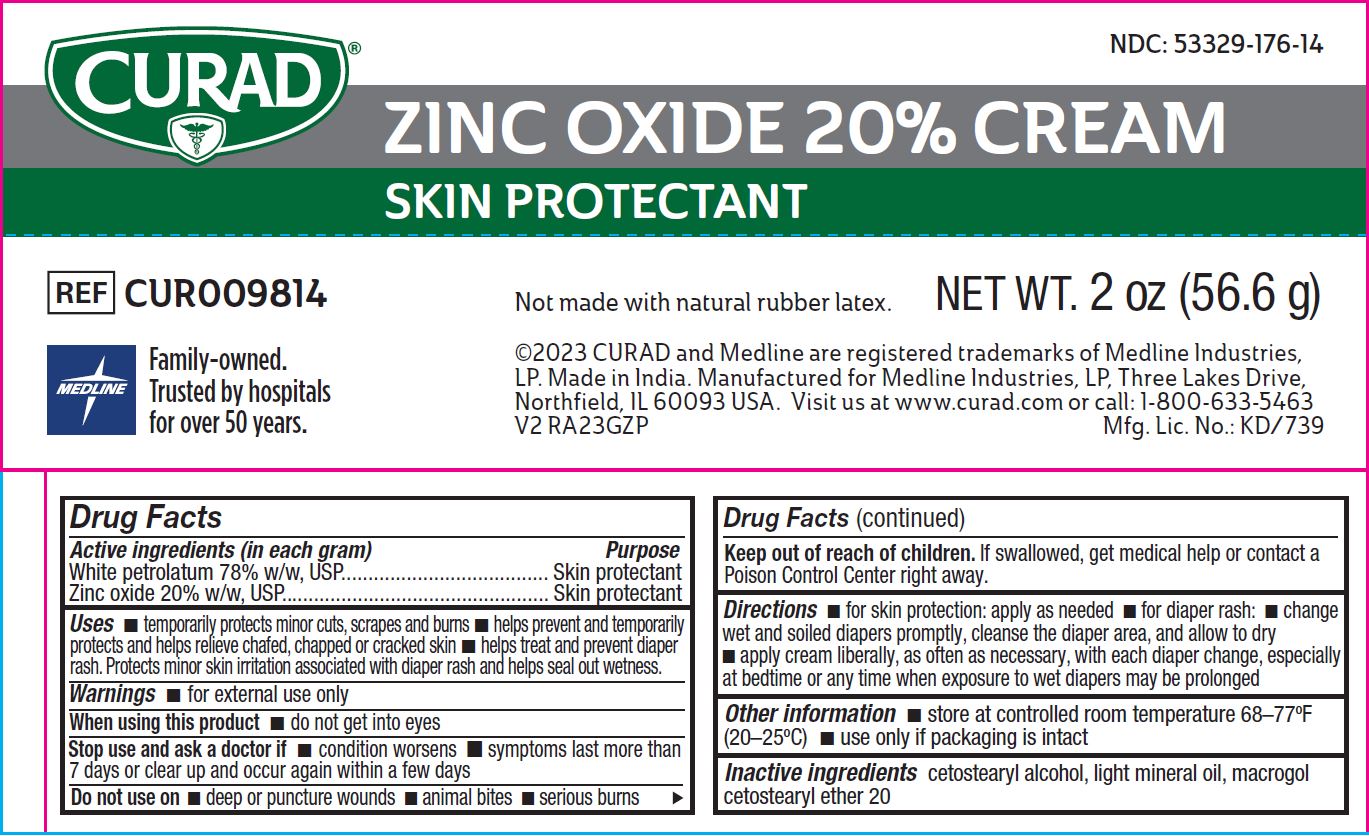 DRUG LABEL: Medline
NDC: 53329-176 | Form: CREAM
Manufacturer: Medline Industries, LP
Category: otc | Type: HUMAN OTC DRUG LABEL
Date: 20251104

ACTIVE INGREDIENTS: ZINC OXIDE 20 g/100 g; PETROLATUM 78 g/100 g
INACTIVE INGREDIENTS: POLYOXYL 20 CETOSTEARYL ETHER; CETOSTEARYL ALCOHOL; LIGHT MINERAL OIL

176 Curad Zinc Oxide Cream CUR009814

Active ingredients (in each gram)

- White petrolatum 78% w/w, USP
- Zinc oxide 20% w/w, USP

Purpose

- Skin protectant

Uses

- temporarily protects minor cuts, scrapes and burns
- helps prevent and temporarily protects and helps relieve chafed, chapped or cracked skin
- helps treat and prevent diaper rash. Protects minor skin irritation associated with diaper rash and helps seal out wetness

Warnings

for external use only

When using this product

- do not get into eyes

Stop use and ask a doctor if

- condition worsens
- symptoms last more than 7 days or clear up and occur again within a few days

Do not use on

- deep or puncture wounds
- animal bites
- serious burns

Keep out of reach of children.

If swallowed, get medical help or contact a Poison Control Center right away.

Directions

- for skin protection: apply as needed
- for diaper rash: change wet and soiled diapers promptly, cleanse the diaper area, and allow to dry
- apply cream liberally, as often as necessary, with each diaper change, especially at bedtime or any time when exposure to wet diapers may be prolonged

Other information

- store at controlled room temperature 68-77°F (20-25°C)
- use only if packaging is intact

Inactive ingredients

cetostearyl alcohol, light mineral oil, macrogol cetostearyl ether 20

Manufacturing information

©2023 CURAD and Medline are

registered trademarks of Medline Industries, LP

Made in India

Manufactured for Medline Industries, LP

Three Lakes Drive, Northfield, IL 60093 USA

Visit www.curad.com or call 1-800-633-5463

REF: CUR009814